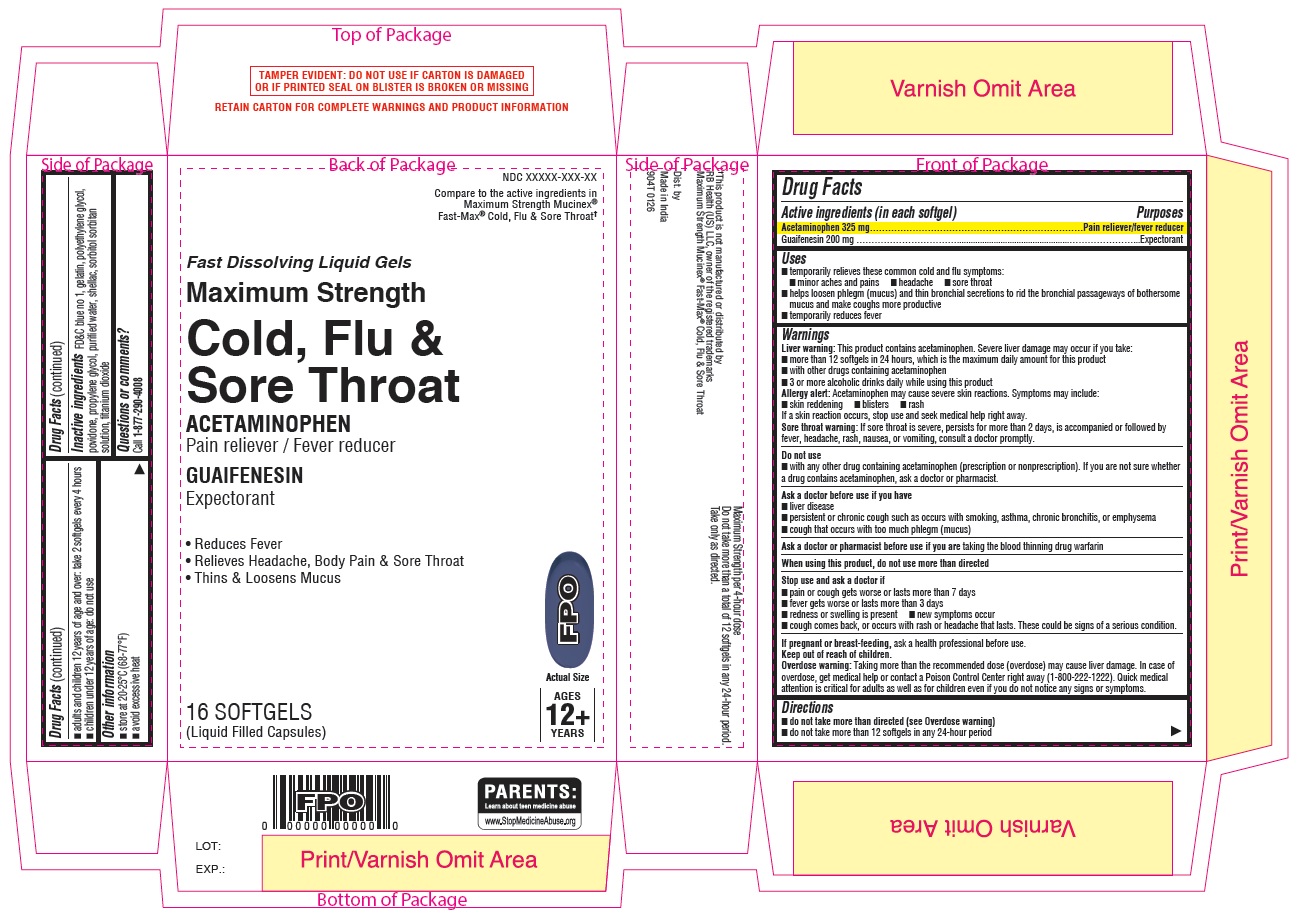 DRUG LABEL: Daytime
NDC: 51316-940 | Form: CAPSULE, LIQUID FILLED
Manufacturer: CVS HEALTH CORP
Category: otc | Type: HUMAN OTC DRUG LABEL
Date: 20260129

ACTIVE INGREDIENTS: ACETAMINOPHEN 325 mg/1 1; GUAIFENESIN 200 mg/1 1
INACTIVE INGREDIENTS: GELATIN, UNSPECIFIED; SORBITAN; SORBITOL SOLUTION; WATER; SHELLAC; TITANIUM DIOXIDE; POLYETHYLENE GLYCOL, UNSPECIFIED; POVIDONE, UNSPECIFIED; PROPYLENE GLYCOL; FD&C BLUE NO. 1

CVS 904T Daytime Softgels

Drug Facts

Active ingredients (in each softgel)

Acetaminophen 325 mg

Dextromethorphan HBr 10 mg

Purposes

Pain reliever/fever reducer

Cough suppressant

Uses

- temporarily relieves these common cold and flu symptoms:

- cough due to minor throat and bronchial irritation as may occur with the common cold or inhaled irritants

- the intensity of coughing

- the impulse to cough to help you get to sleep

- minor aches and pains

- sore throat

- headache

- temporarily reduces fever

Warnings

Liver warning: This product contains acetaminophen. Severe liver damage may occur if you take:

- more than 12 softgels in 24 hours, which is the maximum daily amount for this product
- with other drugs containing acetaminophen
- 3 or more alcoholic drinks daily while using this product

Allergy alert: Acetaminophen may cause severe skin reactions. Symptoms may include:

- skin reddening
- blisters
- rash

If a skin reaction occurs, stop use and seek medical help right away.

Sore throat warning: If sore throat is severe, persists for more than 2 days, is accompanied or followed by fever, headache, rash, nausea, or vomiting, consult a doctor promptly.

Do not use

- with any other drug containing acetaminophen (prescription or nonprescription). If you are not sure whether a drug contains acetaminophen, ask a doctor or pharmacist.
- if you are now taking a prescription monoamine oxidase inhibitor (MAOI) (certain drugs for depression, psychiatric, or emotional conditions, or Parkinson’s disease), or for 2 weeks after stopping the MAOI drug. If you do not know if your prescription drug contains an MAOI, ask a doctor or pharmacist before taking this product.

Ask a doctor before use if you have

- liver disease
- persistent or chronic cough such as occurs with smoking, asthma, or emphysema
- cough that occurs with too much phlegm (mucus)

Ask a doctor or pharmacist before use if you are taking the blood thinning drug warfarin

When using this product do not use more than directed

Stop use and ask a doctor if

- pain or cough gets worse or lasts more than 7 days
- fever gets worse or lasts more than 3 days
- redness or swelling is present
- new symptoms occur
- cough comes back or occurs with rash or headache that lasts. These could be signs of a serious condition.

PREGNANCY OR BREAST FEEDING

If pregnant or breast-feeding, ask a health professional before use.

Keep out of reach of children.

Overdose warning: Taking more than the recommended dose (overdose) may cause liver damage. In case of overdose, get medical help or contact a Poison Control Center right away (1-800-222-1222). Quick medical attention is critical for adults as well as for children even if you do not notice any signs or symptoms.

Directions

- do not take more than directed (see Overdose warning)
- do not take more than 12 softgels in any 24-hour period
- adults and children 12 years of age and over: take 2 softgels every 4 hours
- children under 12 years of age: do not use

Other information

- store at 20-25°C (68-77°F)
- avoid excessive heat

Inactive ingredients

FD&C blue no. 1, gelatin, polyethylene glycol, povidone, propylene glycol, purified water, shellac, sorbitol sorbitan solution, titanium dioxide

Questions or comments? Call 1-877-290-4008